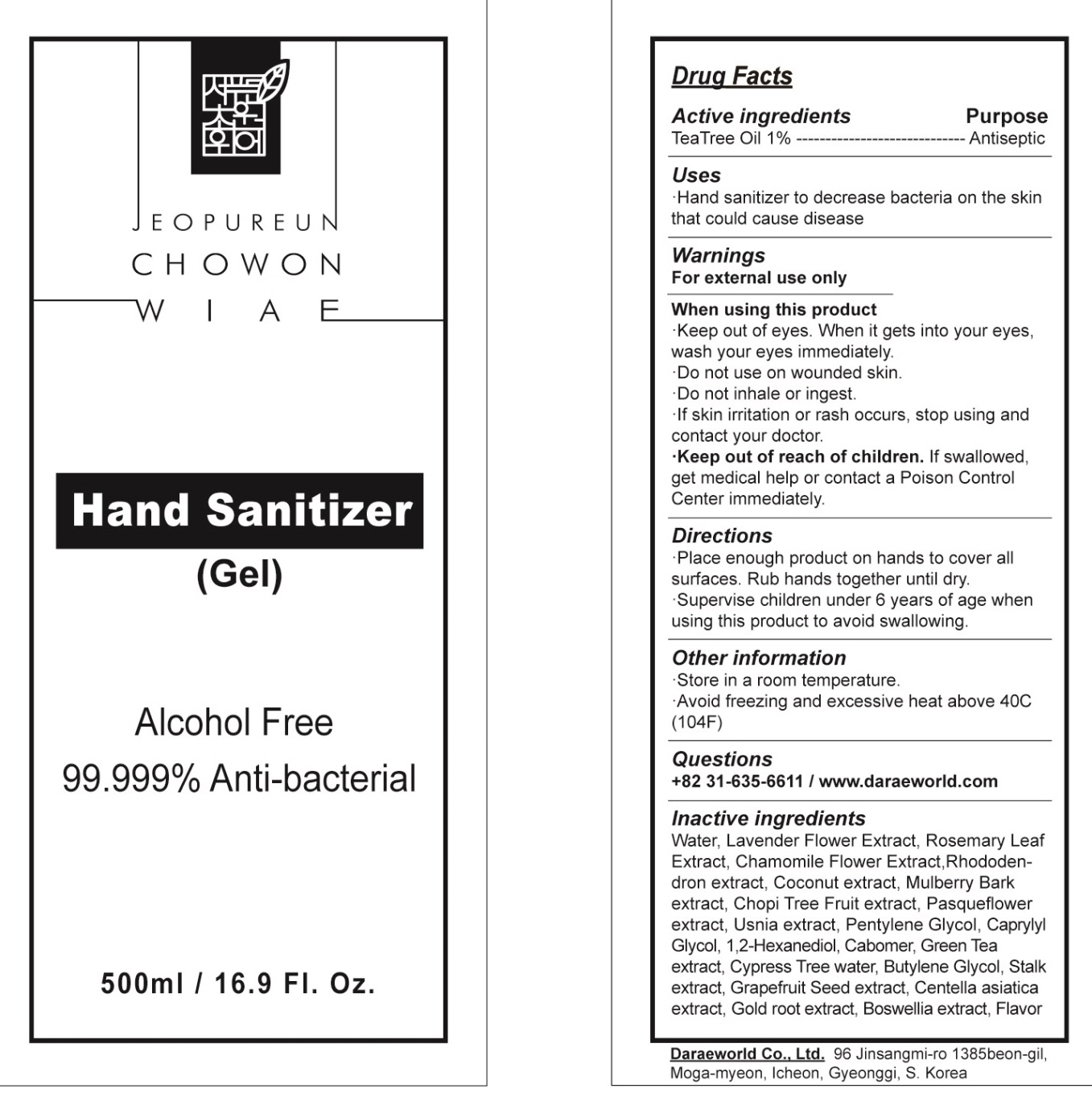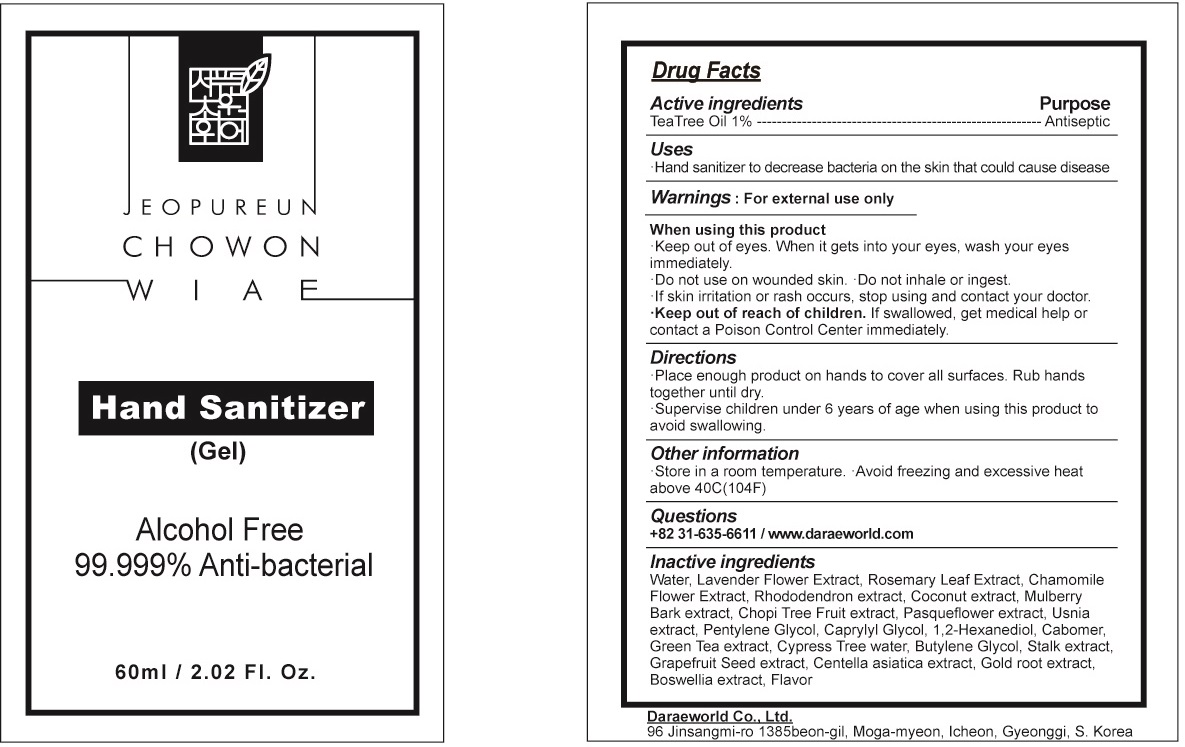 DRUG LABEL: Jeopureun Chowon Wiae Hand sanitizer
NDC: 76593-010 | Form: GEL
Manufacturer: Daraeworld Co., Ltd.
Category: otc | Type: HUMAN OTC DRUG LABEL
Date: 20200428

ACTIVE INGREDIENTS: Tea Tree Oil 1.0 g/100 mL
INACTIVE INGREDIENTS: Water; LAVANDULA ANGUSTIFOLIA SUBSP. ANGUSTIFOLIA FLOWER; ROSEMARY; CHAMAEMELUM NOBILE FLOWER; COCONUT; Pentylene Glycol; Caprylyl Glycol; 1,2-Hexanediol; CARBOMER HOMOPOLYMER, UNSPECIFIED TYPE; GREEN TEA LEAF; Butylene Glycol; CITRUS PARADISI SEED; CENTELLA ASIATICA WHOLE

ACTIVE INGREDIENT

Active ingredients: Tea Tree Oil 1%

INACTIVE INGREDIENT

Inactive Ingredients:

Water, Lavender Flower Extract, Rosemary Leaf Extract, Chamomile Flower Extract, Rhododendron extract, Coconut extract, Mulberry Bark extract, Chopi Tree Fruit extract, Pasqueflower extract, Usnia extract, Pentylene Glycol, Caprylyl Glycol, 1,2-Hexanediol, Cabomer, Green Tea extract, Cypress Tree water, Butylene Glycol, Stalk extract, Grapefruit Seed extract, Centella asiatica extract, Gold root extract, Boswellia extract, Flavor

PURPOSE

Purpose: Antiseptic

WARNINGS

For external use only

When using this product
■ Keep out of eyes. When it gets into your eyes, wash your eyes immediately.
■ Do not use on wounded skin.
■ Do not inhale or ingest.
■ If skin irritation or rash occurs, stop using and contact your doctor.

Keep out of reach of children. If swallowed, get medical help or contact a Poison Control Center immediately.

Uses

■ Hand sanitizer to decrease bacteria on the skin that could cause disease

Directions

■ Place enough product on hands to cover all surfaces. Rub hands together until dry.
■ Supervise children under 6 years of age when using this product to avoid swallowing.

Other Information

■ Store in a room temperature.
■ Avoid freezing and excessive heat above 40C (104F)

Questions

+82 31-635-661 / www.daraeworld.com